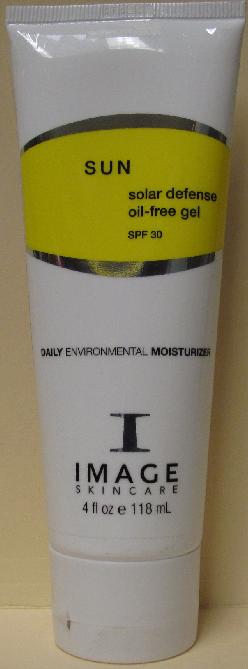 DRUG LABEL: SUN Solar Defense Oil-free SPF 30
NDC: 62742-4040 | Form: GEL
Manufacturer: Allure Labs, Inc.
Category: otc | Type: HUMAN OTC DRUG LABEL
Date: 20100702

ACTIVE INGREDIENTS: ZINC OXIDE 186 mg/1 mL

Drug Facts

Active Ingredients:

Zinc Oxide 18.6%

Purpose:

Sunscreen

Uses:

- An oil-free UVA/UVB brad spectrum daily moisturizer. Provides ultimate protection against the aging effects of the sun and other environmental exposures. Enriched with essential vitamins and ant-oxidants that prevent free radical damage and preserving skin hydration for the entire day.
- Water-resistant
- Paraben-free

Direction:
Apply liberally 15-30 minutes prior to sun exposure. Reapply after prolonged swimming or vigorous activity.
Indications:
Universal for all skin types

Warnings:

For external use only

When using this product

- Keep out of eyes. If contact occurs rinse with water.
- Discontinue use if irritation or redness occurs

Keep out of reach of childrean

Inactive Ingredients:

Water (Aqua), Caprylic/Capric Triglyceride, Glyceryl Stearate, PEG 100 Stearate, Sorbitan Stearate, Citric Acid, Imperata Cylidrica Root Extract, Tocopheryl Linoleate, Lecithin, Xanthan Gum, PEG 8, Ascorbic Acid, Ethylhexylglycerin, Sodium Lactate, Micrococcus Lysate, Arabidopsis Extract, Plankton Extract, Teprenone, Phoenix dactylifera (date) extract, Laureth-7, Disodium EDTA, Dipotassium Glycyrrhizte, Caprylyl Glycol, Tocopherol, Ascorbyl Palmitate, Carbomer

PACKAGE LABEL

Distributor:

Image International

Palm Beach, FL 33411 USA

Image of the product:

SUN Solar Defense Oil-free Gel SPF 30